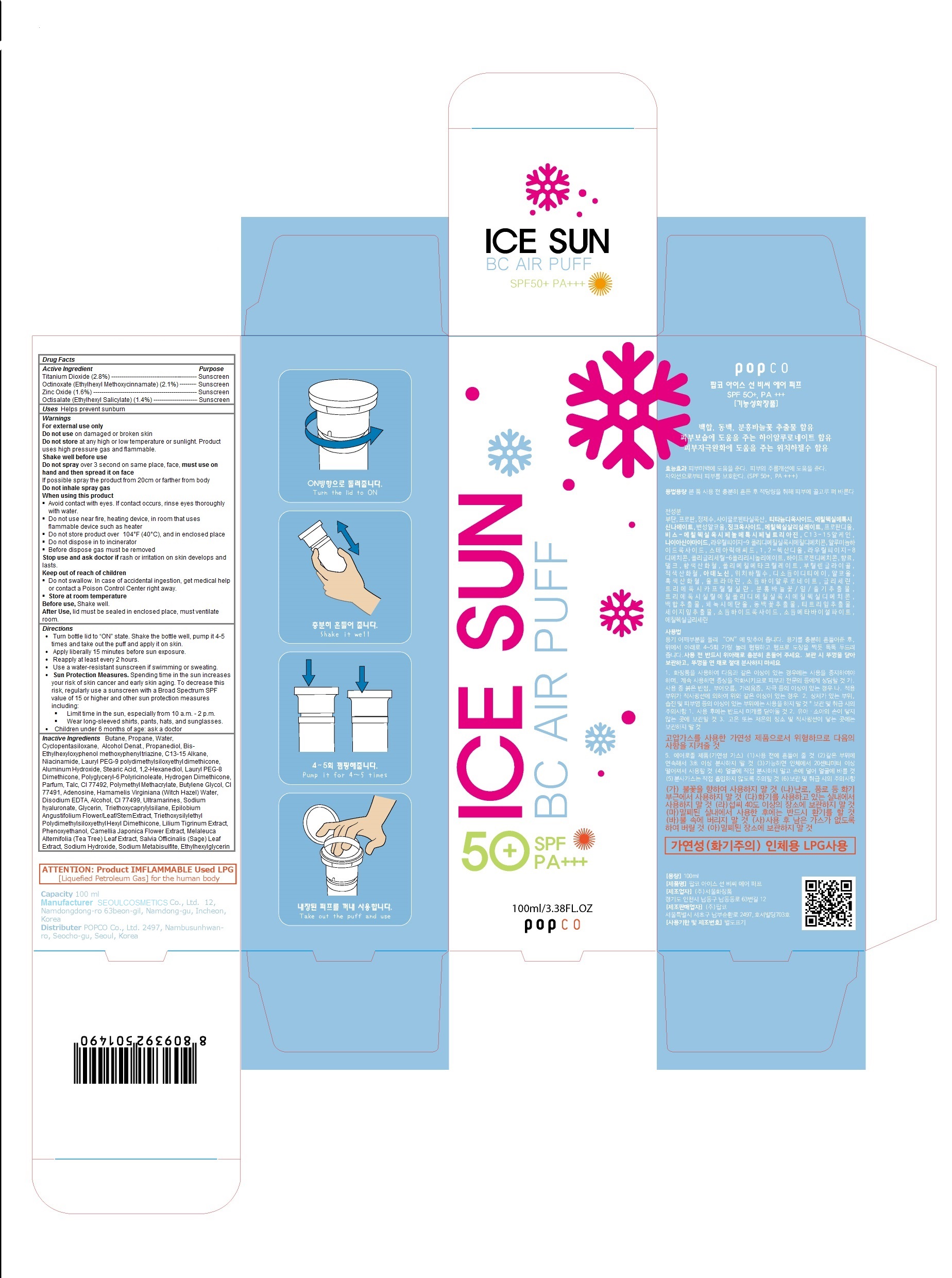 DRUG LABEL: ICE SUN BC AIR PUFF
NDC: 71055-100 | Form: LIQUID
Manufacturer: POPCO CO.,LTD.
Category: otc | Type: HUMAN OTC DRUG LABEL
Date: 20161028

ACTIVE INGREDIENTS: Titanium Dioxide 2.8 g/100 mL; Zinc Oxide 1.6 g/100 mL
INACTIVE INGREDIENTS: Butane; Propane; Water; CYCLOMETHICONE 5; PROPANEDIOL; BEMOTRIZINOL; C13-15 ALKANE; Niacinamide; LAURYL PEG-9 POLYDIMETHYLSILOXYETHYL DIMETHICONE; ALUMINUM HYDROXIDE; Stearic Acid; 1,2-Hexanediol; HYDROGEN DIMETHICONE (13 CST); Talc; FERRIC OXIDE YELLOW; POLY(METHYL METHACRYLATE; 450000 MW); BUTYLENE GLYCOL; FERRIC OXIDE RED; Adenosine; HAMAMELIS VIRGINIANA TOP WATER; EDETATE DISODIUM ANHYDROUS; ALCOHOL; FERROSOFERRIC OXIDE; ULTRAMARINE BLUE; HYALURONATE SODIUM; GLYCERIN; Triethoxycaprylylsilane; EPILOBIUM ANGUSTIFOLIUM FLOWERING TOP; LILIUM LANCIFOLIUM BULB; PHENOXYETHANOL; CAMELLIA JAPONICA FLOWER; MELALEUCA ALTERNIFOLIA LEAF; SAGE; SODIUM HYDROXIDE; Sodium Metabisulfite; ETHYLHEXYLGLYCERIN

ICE SUN BC AIR PUFF

Active Ingredients

Titanium Dioxide (2.8%)

Octinoxate (Ethylhexyl Methoxycinnamate) (2.1%)

Zinc Oxide (1.6%)

Octisalate (Ethylhexyl Salicylate) (1.4%)

Purpose

Sunscreen

Keep out of reach of children

Do not swallow. In case of accidental ingestion, seek professional assistance

Warnings

For external use only
Do not use on damaged or broken skin
Do not store at any high or low temperature or sunlight. Product uses high pressure gas and flammable.
Shake well before use
Do not spray over 3 second on same place, face, must use on hand and then spread it on face
If possible spray the product from 20cm or farther from body
Do not inhale spray gas
When using this product
 Avoid contact with eyes. If contact occurs, rinse eyes thoroughly with water.
 Do not use near fire, heating device, in room that uses flammable device such as heater
 Do not store product over 104°F (40°C), and in enclosed place
 Do not dispose in to incinerator
 Before dispose gas must be removed
Stop use and ask doctor if rash or irritation on skin develops and lasts.

Store at room temperature
Before use, Shake well.
After Use, lid must be sealed in enclosed place, must ventilate room.

Uses

Helps prevent sunburn

Directions

• Turn bottle lid to “ON” state. Shake the bottle well, pump it 4-5 times and take out the puff and apply it on skin.
• Apply liberally 15 minutes before sun exposure.
• Reapply at least every 2 hours.
• Use a water-resistant sunscreen if swimming or sweating.
• Sun Protection Measures. Spending time in the sun increases your risk of skin cancer and early skin aging. To decrease this risk, regularly use a sunscreen with a Broad Spectrum SPF value of 15 or higher and other sun protection measures including:
 Limit time in the sun, especially from 10 a.m. - 2 p.m.
 Wear long-sleeved shirts, pants, hats, and sunglasses.
• Children under 6 months of age: ask a doctor

Inactive Ingredients

Butane, Propane, Water, Cyclopentasiloxane, Alcohol Denat., Propanediol, Bis-Ethylhexyloxyphenol methoxyphenyl triazine, C13-15 Alkane, Niacinamide, Lauryl PEG-9 polydimethylsiloxyethyl dimethicone, Aluminum Hydroxide, Stearic Acid, 1,2-Hexanediol, Lauryl PEG-8 Dimethicone, Polyglyceryl-6 Polyricinoleate, Hydrogen Dimethicone, Parfum, Talc, CI 77492, Polymethyl Methacrylate, Butylene Glycol, CI 77491, Adenosine, Hamamelis Virginiana (Witch Hazel) Water, Disodium EDTA, Alcohol, CI 77499, Ultramarines, Sodium hyaluronate, Glycerin, Triethoxycaprylylsilane, Epilobium Angustifolium Flower/Leaf/Stem Extract, Triethoxysilylethyl Polydimethylsiloxyethyl Hexyl Dimethicone, Lilium Tigrinum Extract, Phenoxyethanol, Camellia Japonica Flower Extract, Melaleuca Alternifolia (Tea Tree) Leaf Extract, Salvia Officinalis (Sage) Leaf Extract, Sodium Hydroxide, Sodium Metabisulfite, Ethylhexylglycerin